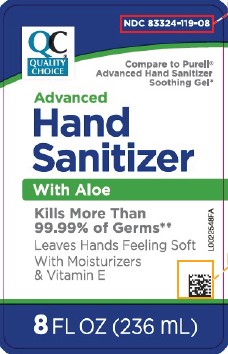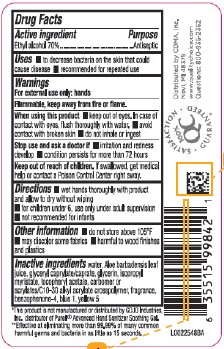 DRUG LABEL: Advanced Hand Sanitizer with Aloe
NDC: 83324-119 | Form: GEL
Manufacturer: Chain Drug Marketing Association
Category: otc | Type: HUMAN OTC DRUG LABEL
Date: 20260223

ACTIVE INGREDIENTS: ALCOHOL 70 mL/100 mL
INACTIVE INGREDIENTS: WATER; ALOE VERA LEAF JUICE; GLYCERYL MONOCAPRYLOCAPRATE; GLYCERIN; ISOPROPYL MYRISTATE; .ALPHA.-TOCOPHEROL ACETATE; CARBOMER HOMOPOLYMER, UNSPECIFIED TYPE; ACRYLATES/C10-30 ALKYL ACRYLATE CROSSPOLYMER (60000 MPA.S); SULISOBENZONE; FD&C BLUE NO. 1; FD&C YELLOW NO. 5

Quality Choice 439.001/439AC
Advanced Hand Sanitizer with Aloe

Active ingredient

Ethyl alcohol 70% {v/v}

Purpose

Antiseptic

Uses

- to decrease bacteria on the skin that could cause disease
- recommended for repeated use

Warnings

For external use only: hands

Flammable, keep away from fire or flame.

When using this product

- keep out of eyes. In case of contact with eyes, flush thoroughly with water.
- avoid contact with broken skin
- do not inhale or ingest

Stop use and ask a doctor if

- irritation and redness develop
- condition persists for more than 72 hours

Keep out of reach of children.

If swallowed, get medical help or contact a Poison Control Center right away.

Directions

- wet hands thoroughly with product and allow to dry without wiping
- for children under 6, use only under adult supervision
- not recommended for infants

Other information

- do not store above 105⁰ F
- may discolor some fabrics
- harmful to wood finishes and plastics

Inactive ingredients

water, Aloe barbadensis leaf juice, glyceryl caprylate/caprate, glycerin, isopropyl myristate, tocopheryl acetate, carbomer or acrylates/C10-30 alkyl acrylate crosspolymer, fragrance, benzophenone-4, blue 1, yellow 5

Disclaimer

*This product is not manufactured or distributed by GOJO Industries, Inc., distributor of Purell®Advanced Hand Sanitizer Soothing Gel.

Claims

**Effective at eliminating more than 99.99% of many common harmful germs and bacteria in as little as 15 seconds.

Adverse Reaction

Distributed by CDMA, Inc.

Novi, MI 48375

www.qualitychoice.com

Questions: 800-935-2362

100% QC SATISFACTION GUARANTEED.

Principal Display Panel

NDC 83324-119-08

QC®

QUALITY CHOICE

Compare to Purell®Advanced Hand Sanitizer Soothing Gel*

Advanced Hand Sanitizer

With Aloe

Kills More Than 99.99% of Germs**

Leaves Hands Feeling Soft

With Moisturizers & Vitamin E

8 FL OZ (236 mL)